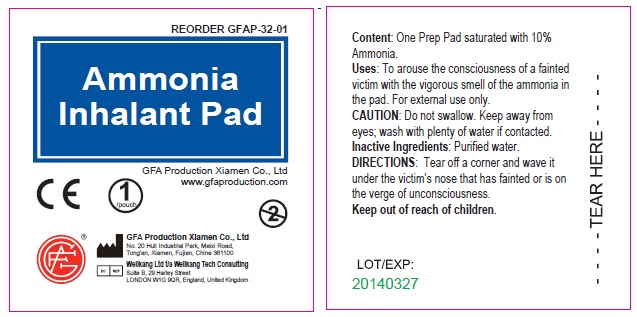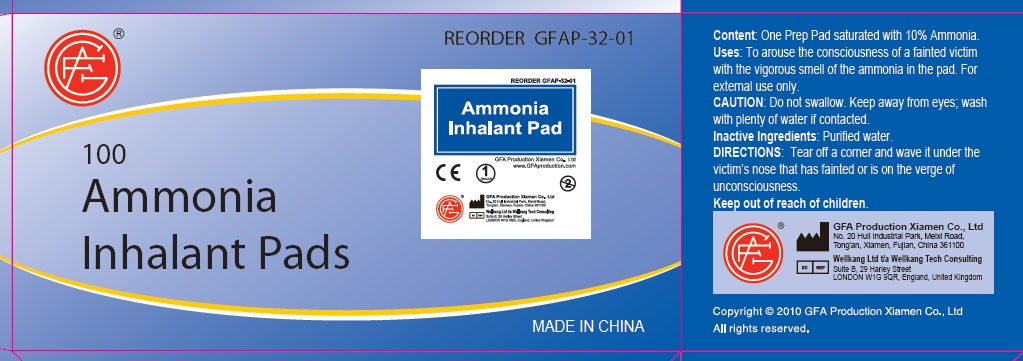 DRUG LABEL: Ammonia Pad
NDC: 52124-3201 | Form: INHALANT
Manufacturer: Genuine First Aid, LLC
Category: otc | Type: HUMAN OTC DRUG LABEL
Date: 20110404

ACTIVE INGREDIENTS: AMMONIA 10 mL/100 mL
INACTIVE INGREDIENTS: WATER

Ammonia Inhalant Pad

Content

One prep pad saturated with 10% ammonia

Purpose

prevent or treat fainting

Uses

Uses to arouse the consciousness of a fainted victim with the vigorous smell of the ammonia in the pad. For external use only.

Caution

Do not swallow. Keep away from eyes; wash with plenty of water if contacted.

Inactive Ingredients

Purified water.

Directions

Tear off a corner and wave it under the victim's nose that has fainted or is on the verge of unconsciousness.

Keep out of reach of children

PACKAGE LABEL

Ammonia Inhalant Pad

GFA Production Xiamen Co., Ltd
www.gfaproduction.com

GFA Production Xiamen Co., Ltd
No. 20 Huli Industrial Park, Meixi Road,
Tong'an, Xiamen, Fujian, China 361100
Wellkang Ltd t/a Wellkang Tech Consulting
Suite B, 29 Harley Street
LONDON W1G 9QR, England, United Kingdom